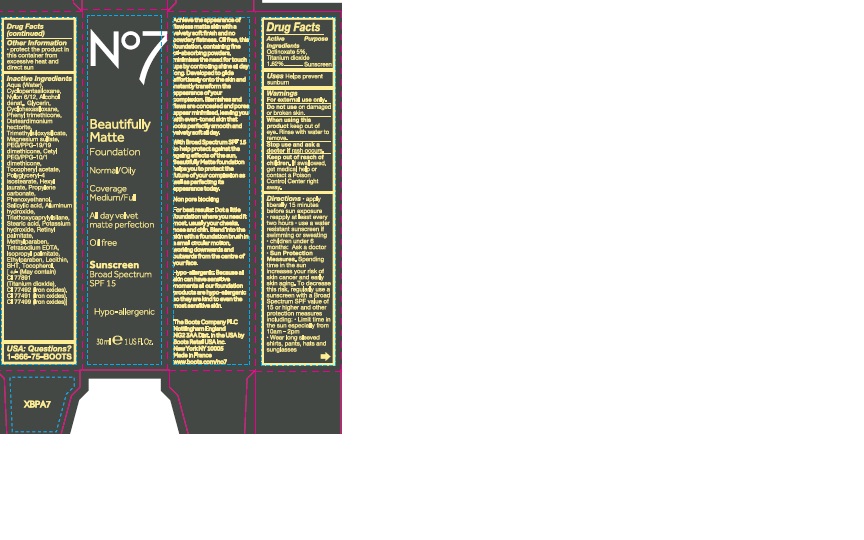 DRUG LABEL: No7 Beautifully Matte Foundation Sunscreen Broad Spectrum SPF 15 Cool Beige
NDC: 61589-8105 | Form: CREAM
Manufacturer: BCM Cosmetique SAS
Category: otc | Type: HUMAN OTC DRUG LABEL
Date: 20241017

ACTIVE INGREDIENTS: Octinoxate 1.5 g/30 g; TITANIUM DIOXIDE 0.5 g/30 g
INACTIVE INGREDIENTS: WATER; CYCLOMETHICONE 5; NYLON 612 (MW 14000); GLYCERIN; CYCLOMETHICONE 6; PHENYL TRIMETHICONE; TRIMETHYLSILOXYSILICATE (M/Q 0.6-0.8); LECITHIN, SOYBEAN; DISTEARDIMONIUM HECTORITE; MAGNESIUM SULFATE, UNSPECIFIED; PEG/PPG-19/19 DIMETHICONE; CETYL PEG/PPG-10/1 DIMETHICONE (HLB 1.5); PHENOXYETHANOL; .ALPHA.-TOCOPHEROL ACETATE; METHYLPARABEN; PROPYLENE CARBONATE; ETHYLPARABEN; SALICYLIC ACID; TRIETHOXYCAPRYLYLSILANE; POTASSIUM HYDROXIDE; TOCOPHEROL; VITAMIN A PALMITATE; ALUMINUM HYDROXIDE; STEARIC ACID; ISOPROPYL PALMITATE; ETIDRONATE TETRASODIUM; FERRIC OXIDE YELLOW; FERRIC OXIDE RED; FERROSOFERRIC OXIDE

No7 Beautifully Matte Foundation Sunscreen Broad Spectrum SPF15 Cool Beige

Carton Active Ingredients Section

Active Ingredients

Octinoxate 5% Titanium dioxide 1.62%

Uses

Uses - helps prevent sunburn

Warnings

For external use only

Do not use on damaged or broken skin

When using this product keep out of eyes. Rinse with water to remove

Warnings

For external use only

Do not use on damaged or broken skin

When using this product keep out of eyes. Rinse with water to remove

Ask a doctor

Stop use and ask a doctor if rash occurs.

Keep out of reach of children. If swallowed, get medical help or contact a Poison Control Center right away.

Directions

Directions for suncreen use

apply liberally 15 minutes before sun exposure

reapply at least every 2 hours

use a water resistant sunscreen if swimming or sweating

children under 6 months of age: Ask a doctor

Sun Protection Measures. Spending time in the sun increases your risk of skin cancer and early skin aging. To decrease this risk, regularly use a sunscreen with a Broad Spectrum SPF value of 15 or higher and other sun protection measures including:

limit time in the sun, especially from 10 a.m. - 2 p.m.

wear long-sleeved shirts, pants, hats, and sunglasses

Directions

Directions for suncreen use

apply liberally 15 minutes before sun exposure

reapply at least every 2 hours

use a water resistant sunscreen if swimming or sweating

children under 6 months of age: Ask a doctor

Sun Protection Measures. Spending time in the sun increases your risk of skin cancer and early skin aging. To decrease this risk, regularly use a sunscreen with a Broad Spectrum SPF value of 15 or higher and other sun protection measures including:

limit time in the sun, especially from 10 a.m. - 2 p.m.

wear long-sleeved shirts, pants, hats, and sunglasses

Other information

Protect the product in this container from excessive heat and direct sun

Inactive ingredients

Aqua(Water), Cyclopentasiloxane, Nylon 6/12, Alcohol denat., Glycerin, Cyclohexasiloxane, Phenyl trimethicone, Disteardimonium hectorite, Trimethylsiloxysilicate, Magnesium sulfate, PEG/PPG-19/19 dimethicone, Cetyl PEG/PPG-10/1 dimethicone, Phenoxyethanol, Tocopheryl acetate, Polyglyceryl-4 isostearate, Hexyl laurate, Propylene carbonate, Salicylic acid, Aluminum hydroxide, Potassium hydroxide, Methylparaben, Ethylparaben, Stearic acid, Triethoxycaprylylsilane, Tetrasodium EDTA, Retinyl palmitate, Isopropyl palmitate, Lecithin, BHT, Tocopherol, , CI 77492(Iron oxides), CI 77891(Titanium dioxide) CI 77491(Iron oxides)CI 77499(Iron oxides)

Description

Beautifully Matte Foundation Normal Oily Coverage Medium/Full All day velvet matte perfection

Achieve the appearance of flawless matte skin with a velvety soft finish and no powdery flatness. Blemishes and flaws are concealed and pores appear minimised, leaving you with even-toned skin that looks perfectly smooth and velvety soft all day.

For best results: dot a little foundation where you need it most, usually your cheeks, nose and chin. Blend into the skin with a foundation brush in a small circular motion, working downwards and outwards from the centre of your face.

Information

The Boots Company PLC

Nottingham England NG2 3AA

Dist. by Boots Retail USA Inc.

New York NY 10005

Made in France

www.boots.com

active ingredients

No7 Beautifully Matte Foundation Sunscreen Broad Spectrum SPF 15

30ml e 1 US Fl.Oz.

Active ingredients: Octinoxate 5.0% Titanium dioxide 1.62%

Warnings

Warning: Avoid contact with eyes. If product gets into the eyes, rinse well with water immediately.

Description

Achieve the appearance of flawless matte skin with a velvety soft finish and no powdery flatness. Oil free, this foundation, containing fine oil-absorbing powders, minimises the need for touch ups by controlling shine all day long. Developed to glide effortlessly onto the skin and instantly transform the appearance of your complexion. Blemishes and flaws are concealed and pores appear minimised, leaving you with even-toned skin that looks perfectly smooth and velvety soft all day.

With Broad Specrtrum SPF 15 to help protect against the ageing effects of the sun, Beautifully Matte foundation helps you to protect the future of your complexion as well as perfecting its appearance today.

Non pore blocking

For best results: Dot a little foundation where you need it most, usually your cheeks, nose and chin. Blend into the skin with a foundation brush in a small circular motion, working downwards and outwards from the centre of your face.

Hypo-allergenic: Because all skin can have sensitive moments all our foundation products are hypo-allergenic so they are kind to even the most sensitive skin.

Information

The Boots Company PLC

Nottingham England NG2 3AA.

Dist. by Boots Retail USA Inc.

New York NY 10005

Made in France

www.boots.com

Carton